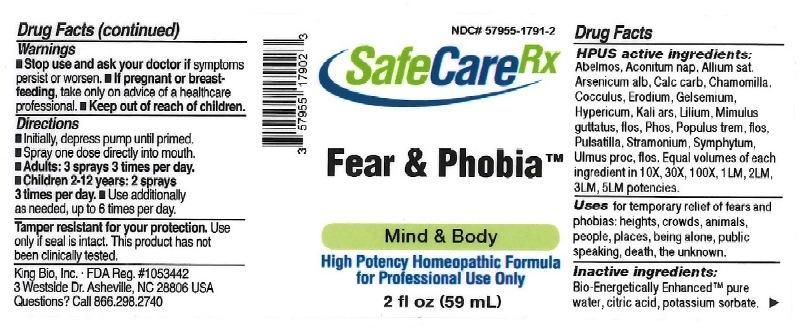 DRUG LABEL: Fear and Phobia
NDC: 57955-1791 | Form: LIQUID
Manufacturer: King Bio Inc.
Category: homeopathic | Type: HUMAN OTC DRUG LABEL
Date: 20161111

ACTIVE INGREDIENTS: ABELMOSCHUS MOSCHATUS SEED 10 [hp_X]/59 mL; ACONITUM NAPELLUS 10 [hp_X]/59 mL; GARLIC 10 [hp_X]/59 mL; ARSENIC TRIOXIDE 10 [hp_X]/59 mL; OYSTER SHELL CALCIUM CARBONATE, CRUDE 10 [hp_X]/59 mL; MATRICARIA RECUTITA 10 [hp_X]/59 mL; ANAMIRTA COCCULUS SEED 10 [hp_X]/59 mL; ERODIUM CICUTARIUM 10 [hp_X]/59 mL; GELSEMIUM SEMPERVIRENS ROOT 10 [hp_X]/59 mL; HYPERICUM PERFORATUM 10 [hp_X]/59 mL; POTASSIUM ARSENITE ANHYDROUS 10 [hp_X]/59 mL; LILIUM LANCIFOLIUM WHOLE FLOWERING 10 [hp_X]/59 mL; MIMULUS GUTTATUS FLOWERING TOP 10 [hp_X]/59 mL; PHOSPHORUS 10 [hp_X]/59 mL; POPULUS TREMULA FLOWERING TOP 10 [hp_X]/59 mL; PULSATILLA VULGARIS 10 [hp_X]/59 mL; DATURA STRAMONIUM 10 [hp_X]/59 mL; COMFREY ROOT 10 [hp_X]/59 mL; ULMUS PROCERA FLOWERING TWIG 10 [hp_X]/59 mL
INACTIVE INGREDIENTS: WATER; ANHYDROUS CITRIC ACID; POTASSIUM SORBATE

Fear and Phobia™

ACTIVE INGREDIENT

Drug Facts__________________________________________________________________________________________________________

HPUS active ingredients: Abelmoschus, Aconitum napellus, Allium sativum, Arsenicum album, Calcarea carbonica, Chamomilla, Cocculus indicus, Erodium, Gelsemium sempervirens, Hypericum perforatum, Kali arsenicosum, Lilium tigrinum, Mimulus guttatus, flos, Phosphorus, Populus tremula, flos, Pulsatilla, Stramonium, Symphytum officinale, Ulmus procera, flos. Equal volumes of each ingredient in 10X, 30X, 100X, 1LM, 2LM, 3LM, 5LM potencies.

INDICATIONS AND USAGE

Uses a natural aid for: fears and phobias including heights, crowds, animals, people, places, being alone, public speaking, death, the unknown.

Inactive Ingredients:

Bio-Energetically Enhanced™ pure water, citric acid and potassium sorbate.

Warnings

- Stop use and ask your doctor if symptoms persist or worsen.
- If pregnant or breast-feeding, take only on advice of a healthcare professional.

- Keep out of reach of children.

Directions

- Initially, depress pump until primed.
- Spray one dose directly into mouth.
- Adults: 3 sprays 3 times per day.
- Children 2-12 years: 2 sprays 3 times per day.
- Use additionally as needed, up to 6 times per day.

OTHER SAFETY INFORMATION

Tamper resistant for your protection. Use only if safety seal is intact. This product has not been clinically tested.

PURPOSE

Uses a natural aid for:

- fears and phobias including heights
- crowds
- animals
- people
- places
- being alone
- public speaking
- death
- the unknown